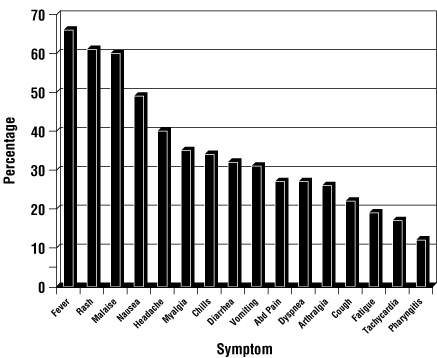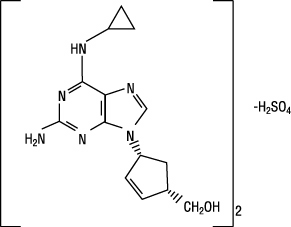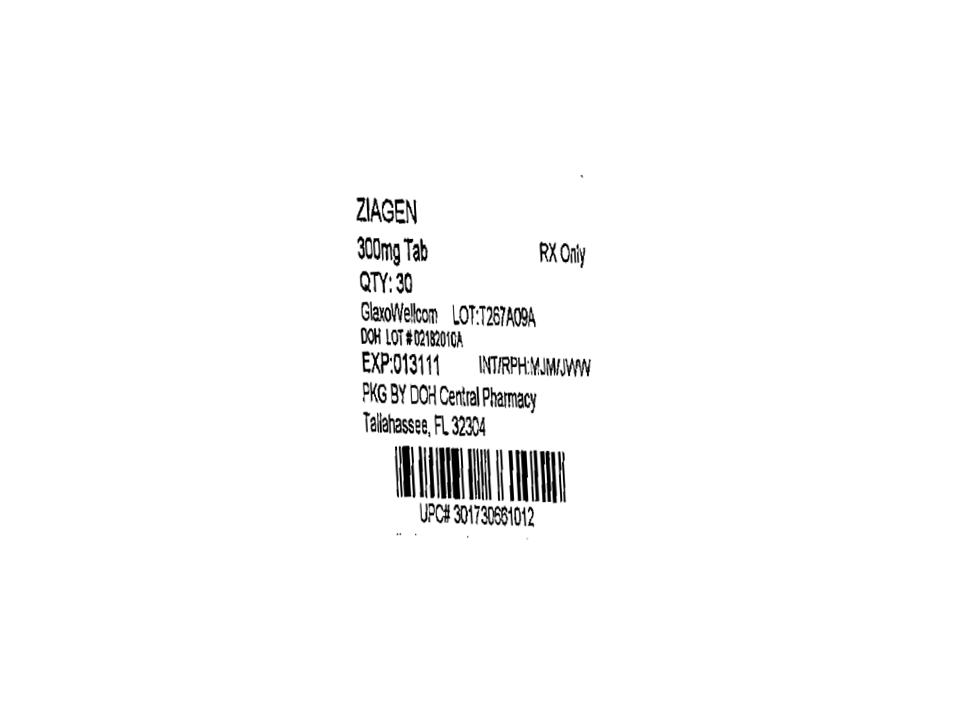 DRUG LABEL: ZIAGEN
NDC: 53808-0811 | Form: TABLET, FILM COATED
Manufacturer: State of Florida DOH Central Pharmacy
Category: prescription | Type: HUMAN PRESCRIPTION DRUG LABEL
Date: 20100413

ACTIVE INGREDIENTS: ABACAVIR SULFATE 300 mg/1 1
INACTIVE INGREDIENTS: COLLOIDAL SILICON DIOXIDE; MAGNESIUM STEARATE; CELLULOSE, MICROCRYSTALLINE; SODIUM STARCH GLYCOLATE TYPE A POTATO; HYPROMELLOSE; POLYSORBATE 80; FERRIC OXIDE YELLOW; TRIACETIN; TITANIUM DIOXIDE

HIGHLIGHTS OF PRESCRIBING INFORMATION

These highlights do not include all the information needed to use ZIAGEN safely and effectively. See full prescribing information for ZIAGEN.
ZIAGEN® (abacavir sulfate) Tablets and Oral Solution
Initial U.S. Approval: 1998

RECENT MAJOR CHANGES

Boxed Warning July 2008

Dosage and Administration (2.2) December 2008

Warnings and Precautions (5.1, 5.5) July 2008

WARNING: RISK OF HYPERSENSITIVITY REACTIONS, LACTIC ACIDOSIS, AND SEVERE HEPATOMEGALY

WARNING: HYPERSENSITIVITY REACTIONS/LACTIC ACIDOSIS AND SEVERE HEPATOMEGALY

See full prescribing information for complete boxed warning.

- Serious and sometimes fatal hypersensitivity reactions have been associated with ZIAGEN (abacavir sulfate). (5.1)
- Hypersensitivity to abacavir is a multi-organ clinical syndrome. (5.1)
- Patients who carry the HLA-B*5701 allele are at high risk for experiencing a hypersensitivity reaction to abacavir. (5.1)
- Discontinue ZIAGEN as soon as a hypersensitivity reaction is suspected. Regardless of HLA-B*5701 status, permanently discontinue ZIAGEN if hypersensitivity cannot be ruled out, even when other diagnoses are possible. (5.1)
- Following a hypersensitivity reaction to abacavir, NEVER restart ZIAGEN or any other abacavir-containing product. (5.1)
- Lactic acidosis and severe hepatomegaly with steatosis, including fatal cases, have been reported with the use of nucleoside analogues. (5.2)

1 INDICATIONS AND USAGE

ZIAGEN, a nucleoside analogue, is indicated in combination with other antiretroviral agents for the treatment of HIV-1 infection. (1)

2 DOSAGE AND ADMINISTRATION

- A medication guide and warning card should be dispensed with each new prescription and refill. (2)
- Adults: 600 mg daily, administered as either 300 mg twice daily or 600 mg once daily. (2.1)
- Pediatric Patients Aged 3 Months and Older: Dose should be calculated on body weight (kg) and should not exceed 300 mg twice daily. (2.2)
- Patients With Hepatic Impairment: Mild hepatic impairment – 200 mg twice daily; moderate/severe hepatic impairment – contraindicated. (2.3)

3 DOSAGE FORMS AND STRENGTHS

Tablets: 300 mg, scored; Oral Solution: 20 mg/mL (3)

4 CONTRAINDICATIONS

- Previously demonstrated hypersensitivity to abacavir. (4, 5.1)
- Moderate or severe hepatic impairment. (4)

5 WARNINGS AND PRECAUTIONS

- Hypersensitivity: Serious and sometimes fatal hypersensitivity reactions have been associated with ZIAGEN and other abacavir-containing products. Read full prescribing information section 5.1 before prescribing ZIAGEN. (5.1)
- Lactic acidosis and severe hepatomegaly with steatosis have been reported with the use of nucleoside analogues. (5.2)
- Immune reconstitution syndrome (5.3) and redistribution/accumulation of body fat have been reported in patients treated with combination antiretroviral therapy. (5.4)

6 ADVERSE REACTIONS

- The most commonly reported adverse reactions of at least moderate intensity (incidence ≥10%) in adult HIV-1 clinical studies were nausea, headache, malaise and fatigue, nausea and vomiting, and dreams/sleep disorders. (6.1)
- The most commonly reported adverse reactions of at least moderate intensity (incidence ≥5%) in pediatric HIV-1 clinical studies were fever and/or chills, nausea and vomiting, skin rashes, and ear/nose/throat infections. (6.1)
  To report SUSPECTED ADVERSE REACTIONS, contact GlaxoSmithKline at 1-888-825-5249 or FDA at 1-800-FDA-1088 or www.fda.gov/medwatch.

7 DRUG INTERACTIONS

- Ethanol: Decreases elimination of abacavir. (7)
- Methadone: An increased methadone dose may be required in a small number of patients. (7)

Revised: December 2008

ZGN:2PI

FULL PRESCRIBING INFORMATION

WARNING: RISK OF HYPERSENSITIVITY REACTIONS, LACTIC ACIDOSIS, AND SEVERE HEPATOMEGALY

Serious and sometimes fatal hypersensitivity reactions have been associated with ZIAGEN (abacavir sulfate).

Hypersensitivity to abacavir is a multi-organ clinical syndrome usually characterized by a sign or symptom in 2 or more of the following groups: (1) fever, (2) rash, (3) gastrointestinal (including nausea, vomiting, diarrhea, or abdominal pain), (4) constitutional (including generalized malaise, fatigue, or achiness), and (5) respiratory (including dyspnea, cough, or pharyngitis). Discontinue ZIAGEN as soon as a hypersensitivity reaction is suspected.

Patients who carry the HLA-B*5701 allele are at high risk for experiencing a hypersensitivity reaction to abacavir. Prior to initiating therapy with abacavir, screening for the HLA-B*5701 allele is recommended; this approach has been found to decrease the risk of hypersensitivity reaction. Screening is also recommended prior to reinitiation of abacavir in patients of unknown HLA-B*5701 status who have previously tolerated abacavir. HLA-B*5701-negative patients may develop a suspected hypersensitivity reaction to abacavir; however, this occurs significantly less frequently than in HLA-B*5701-positive patients.

Regardless of HLA-B*5701 status, permanently discontinue ZIAGEN if hypersensitivity cannot be ruled out, even when other diagnoses are possible.

Following a hypersensitivity reaction to abacavir, NEVER restart ZIAGEN or any other abacavir-containing product because more severe symptoms can occur within hours and may include life-threatening hypotension and death.

Reintroduction of ZIAGEN or any other abacavir-containing product, even in patients who have no identified history or unrecognized symptoms of hypersensitivity to abacavir therapy, can result in serious or fatal hypersensitivity reactions. Such reactions can occur within hours [see Warnings and Precautions (5.1)].

Lactic acidosis and severe hepatomegaly with steatosis, including fatal cases, have been reported with the use of nucleoside analogues alone or in combination, including ZIAGEN and other antiretrovirals [see Warnings and Precautions (5.2)].

1 INDICATIONS AND USAGE

ZIAGEN Tablets and Oral Solution, in combination with other antiretroviral agents, are indicated for the treatment of human immunodeficiency virus (HIV-1) infection.

Additional important information on the use of ZIAGEN for treatment of HIV-1 infection:

- ZIAGEN is one of multiple products containing abacavir. Before starting ZIAGEN, review medical history for prior exposure to any abacavir-containing product in order to avoid reintroduction in a patient with a history of hypersensitivity to abacavir.

2 DOSAGE AND ADMINISTRATION

- A Medication Guide and Warning Card that provide information about recognition of hypersensitivity reactions should be dispensed with each new prescription and refill. To facilitate reporting of hypersensitivity reactions and collection of information on each case, an Abacavir Hypersensitivity Registry has been established. Physicians should register patients by calling 1-800-270-0425.
- ZIAGEN may be taken with or without food.

2.1 Adult Patients

The recommended oral dose of ZIAGEN for adults is 600 mg daily, administered as either 300 mg twice daily or 600 mg once daily, in combination with other antiretroviral agents.

2.2 Pediatric Patients

The recommended oral dose of ZIAGEN Oral Solution in HIV-1-infected pediatric patients aged 3 months and older is 8 mg/kg twice daily (up to a maximum of 300 mg twice daily) in combination with other antiretroviral agents.

ZIAGEN is also available as a scored tablet for HIV-1-infected pediatric patients weighing greater than or equal to 14 kg for whom a solid dosage form is appropriate. Before prescribing ZIAGEN Tablets, children should be assessed for the ability to swallow tablets. If a child is unable to reliably swallow ZIAGEN Tablets, the oral solution formulation should be prescribed. The recommended oral dosage of ZIAGEN Tablets for HIV-1-infected pediatric patients is presented in Table 1.

Table 1. Dosing Recommendations for ZIAGEN Tablets in Pediatric Patients
Weight; (kg) | Dosage Regimen Using Scored Tablet |  | Total; Daily Dose
Weight; (kg) | AM Dose | PM Dose | Total; Daily Dose
14 to 21 | ½ tablet (150 mg) | ½ tablet (150 mg) | 300 mg
>21 to <30 | ½ tablet (150 mg) | 1 tablet (300 mg) | 450 mg
≥30 | 1 tablet (300 mg) | 1 tablet (300 mg) | 600 mg

2.3 Patients with Hepatic Impairment

The recommended dose of ZIAGEN in patients with mild hepatic impairment (Child-Pugh score 5 to 6) is 200 mg twice daily. To enable dose reduction, ZIAGEN Oral Solution (10 mL twice daily) should be used for the treatment of these patients. The safety, efficacy, and pharmacokinetic properties of abacavir have not been established in patients with moderate to severe hepatic impairment; therefore, ZIAGEN is contraindicated in these patients.

3 DOSAGE FORMS AND STRENGTHS

ZIAGEN Tablets, containing abacavir sulfate equivalent to 300 mg abacavir, are yellow, biconvex, scored, capsule-shaped, film-coated, and imprinted with “GX 623” on both sides.

ZIAGEN Oral Solution, each mL containing abacavir sulfate equivalent to 20 mg of abacavir, is a clear to opalescent, yellowish, strawberry-banana-flavored liquid.

4 CONTRAINDICATIONS

ZIAGEN is contraindicated in patients with previously demonstrated hypersensitivity to abacavir or any other component of the products. NEVER restart ZIAGEN or any other abacavir-containing product following a hypersensitivity reaction to abacavir, regardless of HLA-B*5701 status [see Warnings and Precautions (5.1), Adverse Reactions (6)].

ZIAGEN is contraindicated in patients with moderate or severe hepatic impairment.

5 WARNINGS AND PRECAUTIONS

5.1 Hypersensitivity Reaction

Serious and sometimes fatal hypersensitivity reactions have been associated with ZIAGEN and other abacavir-containing products. Patients who carry the HLA-B*5701 allele are at high risk for experiencing a hypersensitivity reaction to abacavir. Prior to initiating therapy with abacavir, screening for the HLA-B*5701 allele is recommended; this approach has been found to decrease the risk of a hypersensitivity reaction. Screening is also recommended prior to reinitiation of abacavir in patients of unknown HLA-B*5701 status who have previously tolerated abacavir. For HLA-B*5701-positive patients, treatment with an abacavir-containing regimen is not recommended and should be considered only with close medical supervision and under exceptional circumstances when the potential benefit outweighs the risk.

HLA-B*5701-negative patients may develop a hypersensitivity reaction to abacavir; however, this occurs significantly less frequently than in HLA-B*5701-positive patients. Regardless of HLA-B*5701 status, permanently discontinue ZIAGEN if hypersensitivity cannot be ruled out, even when other diagnoses are possible.

Important information on signs and symptoms of hypersensitivity, as well as clinical management, is presented below.

Signs and Symptoms of Hypersensitivity: Hypersensitivity to abacavir is a multi-organ clinical syndrome usually characterized by a sign or symptom in 2 or more of the following groups.

Group 1: Fever

Group 2: Rash

Group 3: Gastrointestinal (including nausea, vomiting, diarrhea, or abdominal pain)

Group 4: Constitutional (including generalized malaise, fatigue, or achiness)

Group 5: Respiratory (including dyspnea, cough, or pharyngitis).

Hypersensitivity to abacavir following the presentation of a single sign or symptom has been reported infrequently.

Hypersensitivity to abacavir was reported in approximately 8% of 2,670 patients (n = 206) in 9 clinical trials (range: 2% to 9%) with enrollment from November 1999 to February 2002. Data on time to onset and symptoms of suspected hypersensitivity were collected on a detailed data collection module. The frequencies of symptoms are shown in Figure 1. Symptoms usually appeared within the first 6 weeks of treatment with abacavir, although the reaction may occur at any time during therapy. Median time to onset was 9 days; 89% appeared within the first 6 weeks; 95% of patients reported symptoms from 2 or more of the 5 groups listed above.

Figure 1. Hypersensitivity-Related Symptoms Reported With ≥10% Frequency in Clinical Trials (n = 206 Patients)

Other less common signs and symptoms of hypersensitivity include lethargy, myolysis, edema, abnormal chest x-ray findings (predominantly infiltrates, which can be localized), and paresthesia. Anaphylaxis, liver failure, renal failure, hypotension, adult respiratory distress syndrome, respiratory failure, and death have occurred in association with hypersensitivity reactions. In one study, 4 patients (11%) receiving ZIAGEN 600 mg once daily experienced hypotension with a hypersensitivity reaction compared with 0 patients receiving ZIAGEN 300 mg twice daily.

Physical findings associated with hypersensitivity to abacavir in some patients include lymphadenopathy, mucous membrane lesions (conjunctivitis and mouth ulcerations), and rash. The rash usually appears maculopapular or urticarial, but may be variable in appearance. There have been reports of erythema multiforme. Hypersensitivity reactions have occurred without rash.

Laboratory abnormalities associated with hypersensitivity to abacavir in some patients include elevated liver function tests, elevated creatine phosphokinase, elevated creatinine, and lymphopenia.

Clinical Management of Hypersensitivity: Discontinue ZIAGEN as soon as a hypersensitivity reaction is suspected. To minimize the risk of a life-threatening hypersensitivity reaction, permanently discontinue ZIAGEN if hypersensitivity cannot be ruled out, even when other diagnoses are possible (e.g., acute onset respiratory diseases such as pneumonia, bronchitis, pharyngitis, or influenza; gastroenteritis; or reactions to other medications).

Following a hypersensitivity reaction to abacavir, NEVER restart ZIAGEN or any other abacavir-containing product because more severe symptoms can occur within hours and may include life-threatening hypotension and death.

When therapy with ZIAGEN has been discontinued for reasons other than symptoms of a hypersensitivity reaction, and if reinitiation of ZIAGEN or any other abacavir-containing product is under consideration, carefully evaluate the reason for discontinuation of ZIAGEN to ensure that the patient did not have symptoms of a hypersensitivity reaction. If the patient is of unknown HLA-B*5701 status, screening for the allele is recommended prior to reinitiation of ZIAGEN.

If hypersensitivity cannot be ruled out, DO NOT reintroduce ZIAGEN or any other abacavir-containing product. Even in the absence of the HLA-B*5701 allele, it is important to permanently discontinue abacavir and not rechallenge with abacavir if a hypersensitivity reaction cannot be ruled out on clinical grounds, due to the potential for a severe or even fatal reaction.

If symptoms consistent with hypersensitivity are not identified, reintroduction can be undertaken with continued monitoring for symptoms of a hypersensitivity reaction. Make patients aware that a hypersensitivity reaction can occur with reintroduction of ZIAGEN or any other abacavir-containing product and that reintroduction of ZIAGEN or any other abacavir-containing product needs to be undertaken only if medical care can be readily accessed by the patient or others.

Risk Factor: HLA-B*5701 Allele: Studies have shown that carriage of the HLA-B*5701 allele is associated with a significantly increased risk of a hypersensitivity reaction to abacavir.

CNA106030 (PREDICT-1), a randomized, double-blind study, evaluated the clinical utility of prospective HLA-B*5701 screening on the incidence of abacavir hypersensitivity reaction in abacavir-naive HIV-1-infected adults (n = 1,650). In this study, use of pre-therapy screening for the HLA-B*5701 allele and exclusion of subjects with this allele reduced the incidence of clinically suspected abacavir hypersensitivity reactions from 7.8% (66/847) to 3.4% (27/803). Based on this study, it is estimated that 61% of patients with the HLA-B*5701 allele will develop a clinically suspected hypersensitivity reaction during the course of abacavir treatment compared with 4% of patients who do not have the HLA-B*5701 allele.

Screening for carriage of the HLA -B*5701 allele is recommended prior to initiating treatment with abacavir. Screening is also recommended prior to reinitiation of abacavir in patients of unknown HLA-B*5701 status who have previously tolerated abacavir. For HLA-B*5701-positive patients, initiating or reinitiating treatment with an abacavir-containing regimen is not recommended and should be considered only with close medical supervision and under exceptional circumstances where potential benefit outweighs the risk.

Skin patch testing is used as a research tool and should not be used to aid in the clinical diagnosis of abacavir hypersensitivity.

In any patient treated with abacavir, the clinical diagnosis of hypersensitivity reaction must remain the basis of clinical decision-making. Even in the absence of the HLA-B*5701 allele, it is important to permanently discontinue abacavir and not rechallenge with abacavir if a hypersensitivity reaction cannot be ruled out on clinical grounds, due to the potential for a severe or even fatal reaction.

Abacavir Hypersensitivity Reaction Registry: An Abacavir Hypersensitivity Registry has been established to facilitate reporting of hypersensitivity reactions and collection of information on each case. Physicians should register patients by calling 1-800-270-0425.

5.2 Lactic Acidosis/Severe Hepatomegaly With Steatosis

Lactic acidosis and severe hepatomegaly with steatosis, including fatal cases, have been reported with the use of nucleoside analogues alone or in combination, including abacavir and other antiretrovirals. A majority of these cases have been in women. Obesity and prolonged nucleoside exposure may be risk factors. Particular caution should be exercised when administering ZIAGEN to any patient with known risk factors for liver disease; however, cases have also been reported in patients with no known risk factors. Treatment with ZIAGEN should be suspended in any patient who develops clinical or laboratory findings suggestive of lactic acidosis or pronounced hepatotoxicity (which may include hepatomegaly and steatosis even in the absence of marked transaminase elevations).

5.3 Immune Reconstitution Syndrome

Immune reconstitution syndrome has been reported in patients treated with combination antiretroviral therapy, including ZIAGEN. During the initial phase of combination antiretroviral treatment, patients whose immune systems respond may develop an inflammatory response to indolent or residual opportunistic infections (such as Mycobacterium avium infection, cytomegalovirus, Pneumocystis jirovecii pneumonia [PCP], or tuberculosis), which may necessitate further evaluation and treatment.

5.4 Fat Redistribution

Redistribution/accumulation of body fat including central obesity, dorsocervical fat enlargement (buffalo hump), peripheral wasting, facial wasting, breast enlargement, and “cushingoid appearance” have been observed in patients receiving antiretroviral therapy. The mechanism and long-term consequences of these events are currently unknown. A causal relationship has not been established.

5.5 Myocardial Infarction

In a published prospective, observational, epidemiological study designed to investigate the rate of myocardial infarction in patients on combination antiretroviral therapy, the use of abacavir within the previous 6 months was correlated with an increased risk of myocardial infarction (MI).^1 In a sponsor-conducted pooled analysis of clinical trials, no excess risk of myocardial infarction was observed in abacavir-treated subjects as compared with control subjects. In totality, the available data from the observational cohort and from clinical trials are inconclusive.

As a precaution, the underlying risk of coronary heart disease should be considered when prescribing antiretroviral therapies, including abacavir, and action taken to minimize all modifiable risk factors (e.g., hypertension, hyperlipidemia, diabetes mellitus, and smoking).

6 ADVERSE REACTIONS

- Serious and sometimes fatal hypersensitivity reactions have been associated with ZIAGEN (abacavir sulfate). In one study, once-daily dosing of ZIAGEN was associated with more severe hypersensitivity reactions [see Warnings and Precautions (5.1)].

6.1 Clinical Trials Experience

Because clinical trials are conducted under widely varying conditions, adverse reaction rates observed in the clinical trials of a drug cannot be directly compared with rates in the clinical trials of another drug and may not reflect the rates observed in practice.

Adults: Therapy-Naive Adults: Treatment-emergent clinical adverse reactions (rated by the investigator as moderate or severe) with a greater than or equal to 5% frequency during therapy with ZIAGEN 300 mg twice daily, lamivudine 150 mg twice daily, and efavirenz 600 mg daily compared with zidovudine 300 mg twice daily, lamivudine 150 mg twice daily, and efavirenz 600 mg daily from CNA30024 are listed in Table 2.

Table 2. Treatment-Emergent (All Causality) Adverse Reactions of at Least Moderate Intensity (Grades 2-4, ≥5% Frequency) in Therapy-Naive Adults (CNA30024*) Through 48 Weeks of Treatment
Adverse Reaction | ZIAGEN plus Lamivudine plus Efavirenz; (n = 324) | Zidovudine plus Lamivudine plus Efavirenz; (n = 325)
Dreams/sleep disorders | 10% | 10%
Drug hypersensitivity | 9% | <1%†
Headaches/migraine | 7% | 11%
Nausea | 7% | 11%
Fatigue/malaise | 7% | 10%
Diarrhea | 7% | 6%
Rashes | 6% | 12%
Abdominal pain/gastritis/ gastrointestinal signs and symptoms | 6% | 8%
Depressive disorders | 6% | 6%
Dizziness | 6% | 6%
Musculoskeletal pain | 6% | 5%
Bronchitis | 4% | 5%
Vomiting | 2% | 9%
* This study used double-blind ascertainment of suspected hypersensitivity reactions. During the blinded portion of the study, suspected hypersensitivity to abacavir was reported by investigators in 9% of 324 patients in the abacavir group and 3% of 325 patients in the zidovudine group.
† Ten (3%) cases of suspected drug hypersensitivity were reclassified as not being due to abacavir following unblinding.

Treatment-emergent clinical adverse reactions (rated by the investigator as moderate or severe) with a greater than or equal to 5% frequency during therapy with ZIAGEN 300 mg twice daily, lamivudine 150 mg twice daily, and zidovudine 300 mg twice daily compared with indinavir 800 mg 3 times daily, lamivudine 150 mg twice daily, and zidovudine 300 mg twice daily from CNA3005 are listed in Table 3.

Table 3. Treatment-Emergent (All Causality) Adverse Reactions of at Least Moderate Intensity (Grades 2-4, ≥5% Frequency) in Therapy-Naive Adults (CNA3005) Through 48 Weeks of Treatment
Adverse Reaction | ZIAGEN plus Lamivudine/Zidovudine; (n = 262) | Indinavir plus Lamivudine/Zidovudine; (n = 264)
Nausea | 19% | 17%
Headache | 13% | 9%
Malaise and fatigue | 12% | 12%
Nausea and vomiting | 10% | 10%
Hypersensitivity reaction | 8% | 2%
Diarrhea | 7% | 5%
Fever and/or chills | 6% | 3%
Depressive disorders | 6% | 4%
Musculoskeletal pain | 5% | 7%
Skin rashes | 5% | 4%
Ear/nose/throat infections | 5% | 4%
Viral respiratory infections | 5% | 5%
Anxiety | 5% | 3%
Renal signs/symptoms | <1% | 5%
Pain (non-site-specific) | <1% | 5%

Five patients receiving ZIAGEN in CNA3005 experienced worsening of pre-existing depression compared with none in the indinavir arm. The background rates of pre-existing depression were similar in the 2 treatment arms.

ZIAGEN Once Daily Versus ZIAGEN Twice Daily (CNA30021): Treatment-emergent clinical adverse reactions (rated by the investigator as at least moderate) with a greater than or equal to 5% frequency during therapy with ZIAGEN 600 mg once daily or ZIAGEN 300 mg twice daily both in combination with lamivudine 300 mg once daily and efavirenz 600 mg once daily from CNA30021 were similar. For hypersensitivity reactions, patients receiving ZIAGEN once daily showed a rate of 9% in comparison with a rate of 7% for patients receiving ZIAGEN twice daily. However, patients receiving ZIAGEN 600 mg once daily, experienced a significantly higher incidence of severe drug hypersensitivity reactions and severe diarrhea compared with patients who received ZIAGEN 300 mg twice daily. Five percent (5%) of patients receiving ZIAGEN 600 mg once daily had severe drug hypersensitivity reactions compared with 2% of patients receiving ZIAGEN 300 mg twice daily. Two percent (2%) of patients receiving ZIAGEN 600 mg once daily had severe diarrhea while none of the patients receiving ZIAGEN 300 mg twice daily had this event.

Laboratory Abnormalities: Laboratory abnormalities (Grades 3-4) in therapy-naive adults during therapy with ZIAGEN 300 mg twice daily, lamivudine 150 mg twice daily, and efavirenz 600 mg daily compared with zidovudine 300 mg twice daily, lamivudine 150 mg twice daily, and efavirenz 600 mg daily from CNA30024 are listed in Table 4.

Table 4. Laboratory Abnormalities (Grades 3-4) in Therapy-Naive Adults (CNA30024) Through 48 Weeks of Treatment
Grade 3/4; Laboratory Abnormalities | ZIAGEN plus; Lamivudine plus Efavirenz; (n = 324) | Zidovudine plus; Lamivudine plus Efavirenz (n = 325)
Elevated CPK (>4 X ULN) | 8% | 8%
Elevated ALT (>5 X ULN) | 6% | 6%
Elevated AST (>5 X ULN) | 6% | 5%
Hypertriglyceridemia (>750 mg/dL) | 6% | 5%
Hyperamylasemia (>2 X ULN) | 4% | 5%
Neutropenia (ANC <750/mm^3) | 2% | 4%
Anemia (Hgb ≤6.9 gm/dL) | <1% | 2%
Thrombocytopenia (Platelets <50,000/mm^3) | 1% | <1%
Leukopenia (WBC ≤1,500/mm^3) | <1% | 2%
ULN = Upper limit of normal.
n = Number of patients assessed.

Laboratory abnormalities in CNA3005 are listed in Table 5.

Table 5. Treatment-Emergent Laboratory Abnormalities (Grades 3-4) in CNA3005
Grade 3/4 Laboratory Abnormalities | Number of Subjects by Treatment Group
Grade 3/4 Laboratory Abnormalities | ZIAGEN plus; Lamivudine/Zidovudine; (n = 262) | Indinavir plus Lamivudine/Zidovudine; (n = 264)
Elevated CPK (>4 x ULN) | 18 (7%) | 18 (7%)
ALT (>5.0 x ULN) | 16 (6%) | 16 (6%)
Neutropenia (<750/mm^3) | 13 (5%) | 13 (5%)
Hypertriglyceridemia (>750 mg/dL) | 5 (2%) | 3 (1%)
Hyperamylasemia (>2.0 x ULN) | 5 (2%) | 1 (<1%)
Hyperglycemia (>13.9 mmol/L) | 2 (<1%) | 2 (<1%)
Anemia (Hgb ≤6.9 g/dL) | 0 (0%) | 3 (1%)
ULN = Upper limit of normal.
n = Number of patients assessed.

The frequencies of treatment-emergent laboratory abnormalities were comparable between treatment groups in CNA30021.

Pediatric Patients: Therapy-Experienced Pediatric Patients: Treatment-emergent clinical adverse reactions (rated by the investigator as moderate or severe) with a greater than or equal to 5% frequency during therapy with ZIAGEN 8 mg/kg twice daily, lamivudine 4 mg/kg twice daily, and zidovudine 180 mg/m^2 twice daily compared with lamivudine 4 mg/kg twice daily and zidovudine 180 mg/m^2 twice daily from CNA3006 are listed in Table 6.

Table 6. Treatment-Emergent (All Causality) Adverse Reactions of at Least Moderate Intensity (Grades 2-4, ≥5% Frequency) in Therapy-Experienced Pediatric Patients (CNA3006) Through 16 Weeks of Treatment
Adverse Reaction | ZIAGEN plus Lamivudine plus Zidovudine; (n = 102) | Lamivudine plus Zidovudine; (n = 103)
Fever and/or chills | 9% | 7%
Nausea and vomiting | 9% | 2%
Skin rashes | 7% | 1%
Ear/nose/throat infections | 5% | 1%
Pneumonia | 4% | 5%
Headache | 1% | 5%

Laboratory Abnormalities: In Study CNA3006, laboratory abnormalities (anemia, neutropenia, liver function test abnormalities, and CPK elevations) were observed with similar frequencies as in a study of therapy-naive adults (CNA30024). Mild elevations of blood glucose were more frequent in pediatric patients receiving ZIAGEN (CNA3006) as compared with adult patients (CNA30024).

Other Adverse Events: In addition to adverse reactions and laboratory abnormalities reported in Tables 2, 3, 4, 5, and 6, other adverse reactions observed in the expanded access program were pancreatitis and increased GGT.

6.2 Postmarketing Experience

In addition to adverse reactions reported from clinical trials, the following reactions have been identified during postmarketing use of ZIAGEN. Because they are reported voluntarily from a population of unknown size, estimates of frequency cannot be made. These reactions have been chosen for inclusion due to a combination of their seriousness, frequency of reporting, or potential causal connection to ZIAGEN.

Body as a Whole: Redistribution/accumulation of body fat.

Cardiovascular: Myocardial infarction.

Hepatic: Lactic acidosis and hepatic steatosis.

Skin: Suspected Stevens-Johnson syndrome (SJS) and toxic epidermal necrolysis (TEN) have been reported in patients receiving abacavir primarily in combination with medications known to be associated with SJS and TEN, respectively. Because of the overlap of clinical signs and symptoms between hypersensitivity to abacavir and SJS and TEN, and the possibility of multiple drug sensitivities in some patients, abacavir should be discontinued and not restarted in such cases.

There have also been reports of erythema multiforme with abacavir use.

7 DRUG INTERACTIONS

Ethanol: Abacavir has no effect on the pharmacokinetic properties of ethanol. Ethanol decreases the elimination of abacavir causing an increase in overall exposure [see Clinical Pharmacology (12.3)].

Methadone: The addition of methadone has no clinically significant effect on the pharmacokinetic properties of abacavir. In a study of 11 HIV-1-infected patients receiving methadone-maintenance therapy with 600 mg of ZIAGEN twice daily (twice the currently recommended dose), oral methadone clearance increased [see Clinical Pharmacology (12.3)]. This alteration will not result in a methadone dose modification in the majority of patients; however, an increased methadone dose may be required in a small number of patients.

8 USE IN SPECIFIC POPULATIONS

8.1 Pregnancy

Pregnancy Category C. Studies in pregnant rats showed that abacavir is transferred to the fetus through the placenta. Fetal malformations (increased incidences of fetal anasarca and skeletal malformations) and developmental toxicity (depressed fetal body weight and reduced crown-rump length) were observed in rats at a dose which produced 35 times the human exposure, based on AUC. Embryonic and fetal toxicities (increased resorptions, decreased fetal body weights) and toxicities to the offspring (increased incidence of stillbirth and lower body weights) occurred at half of the above-mentioned dose in separate fertility studies conducted in rats. In the rabbit, no developmental toxicity and no increases in fetal malformations occurred at doses that produced 8.5 times the human exposure at the recommended dose based on AUC.

There are no adequate and well-controlled studies in pregnant women. ZIAGEN should be used during pregnancy only if the potential benefits outweigh the risk.

Antiretroviral Pregnancy Registry: To monitor maternal-fetal outcomes of pregnant women exposed to ZIAGEN, an Antiretroviral Pregnancy Registry has been established. Physicians are encouraged to register patients by calling 1-800-258-4263.

8.3 Nursing Mothers

The Centers for Disease Control and Prevention recommend that HIV-1-infected mothers not breastfeed their infants to avoid risking postnatal transmission of HIV-1 infection.

Although it is not known if abacavir is excreted in human milk, abacavir is secreted into the milk of lactating rats. Because of both the potential for HIV-1 transmission and the potential for serious adverse reactions in nursing infants, mothers should be instructed not to breastfeed if they are receiving ZIAGEN.

8.4 Pediatric Use

The safety and effectiveness of ZIAGEN have been established in pediatric patients 3 months to 13 years of age. Use of ZIAGEN in these age groups is supported by pharmacokinetic studies and evidence from adequate and well-controlled studies of ZIAGEN in adults and pediatric patients [see Dosage and Administration (2.2), Clinical Pharmacology (12.3), Clinical Studies (14.2)].

8.5 Geriatric Use

Clinical studies of ZIAGEN did not include sufficient numbers of patients aged 65 and over to determine whether they respond differently from younger patients. In general, dose selection for an elderly patient should be cautious, reflecting the greater frequency of decreased hepatic, renal, or cardiac function, and of concomitant disease or other drug therapy.

10 OVERDOSAGE

There is no known antidote for ZIAGEN. It is not known whether abacavir can be removed by peritoneal dialysis or hemodialysis.

11 DESCRIPTION

ZIAGEN is the brand name for abacavir sulfate, a synthetic carbocyclic nucleoside analogue with inhibitory activity against HIV-1. The chemical name of abacavir sulfate is (1S,cis)-4-[2-amino-6-(cyclopropylamino)-9H-purin-9-yl]-2-cyclopentene-1-methanol sulfate (salt) (2:1). Abacavir sulfate is the enantiomer with 1S, 4R absolute configuration on the cyclopentene ring. It has a molecular formula of (C14H18N6O)2•H2SO4 and a molecular weight of 670.76 daltons. It has the following structural formula:

Abacavir sulfate is a white to off-white solid with a solubility of approximately 77 mg/mL in distilled water at 25°C. It has an octanol/water (pH 7.1 to 7.3) partition coefficient (log P) of approximately 1.20 at 25°C.

ZIAGEN Tablets are for oral administration. Each tablet contains abacavir sulfate equivalent to 300 mg of abacavir as active ingredient and the following inactive ingredients: colloidal silicon dioxide, magnesium stearate, microcrystalline cellulose, and sodium starch glycolate. The tablets are coated with a film that is made of hypromellose, polysorbate 80, synthetic yellow iron oxide, titanium dioxide, and triacetin.

ZIAGEN Oral Solution is for oral administration. Each milliliter (1 mL) of ZIAGEN Oral Solution contains abacavir sulfate equivalent to 20 mg of abacavir (i.e., 20 mg/mL) as active ingredient and the following inactive ingredients: artificial strawberry and banana flavors, citric acid (anhydrous), methylparaben and propylparaben (added as preservatives), propylene glycol, saccharin sodium, sodium citrate (dihydrate), sorbitol solution, and water.

In vivo, abacavir sulfate dissociates to its free base, abacavir. All dosages for ZIAGEN are expressed in terms of abacavir.

12 CLINICAL PHARMACOLOGY

12.1 Mechanism of Action

Abacavir is an antiviral agent [See Clinical Pharmacology (12.4)].

12.3 Pharmacokinetics

Pharmacokinetics in Adults: The pharmacokinetic properties of abacavir have been studied in asymptomatic, HIV-1-infected adult patients after administration of a single intravenous (IV) dose of 150 mg and after single and multiple oral doses. The pharmacokinetic properties of abacavir were independent of dose over the range of 300 to 1,200 mg/day.

Absorption and Bioavailability: Abacavir was rapidly and extensively absorbed after oral administration. The geometric mean absolute bioavailability of the tablet was 83%. After oral administration of 300 mg twice daily in 20 patients, the steady-state peak serum abacavir concentration (Cmax) was 3.0 ± 0.89 mcg/mL (mean ± SD) and AUC(0-12 hr) was 6.02 ± 1.73 mcg•hr/mL. After oral administration of a single dose of 600 mg of abacavir in 20 patients, Cmax was 4.26 ± 1.19 mcg/mL (mean ± SD) and AUC∞ was 11.95 ± 2.51 mcg•hr/mL.

Distribution: The apparent volume of distribution after IV administration of abacavir was 0.86 ± 0.15 L/kg, suggesting that abacavir distributes into extravascular space. In 3 subjects, the CSF AUC(0-6 hr) to plasma abacavir AUC(0-6 hr) ratio ranged from 27% to 33%.

Binding of abacavir to human plasma proteins is approximately 50%. Binding of abacavir to plasma proteins was independent of concentration. Total blood and plasma drug-related radioactivity concentrations are identical, demonstrating that abacavir readily distributes into erythrocytes.

Metabolism: In humans, abacavir is not significantly metabolized by cytochrome P450 enzymes. The primary routes of elimination of abacavir are metabolism by alcohol dehydrogenase (to form the 5′-carboxylic acid) and glucuronyl transferase (to form the 5′-glucuronide). The metabolites do not have antiviral activity. In vitro experiments reveal that abacavir does not inhibit human CYP3A4, CYP2D6, or CYP2C9 activity at clinically relevant concentrations.

Elimination: Elimination of abacavir was quantified in a mass balance study following administration of a 600-mg dose of ^14C-abacavir: 99% of the radioactivity was recovered, 1.2% was excreted in the urine as abacavir, 30% as the 5′-carboxylic acid metabolite, 36% as the 5′-glucuronide metabolite, and 15% as unidentified minor metabolites in the urine. Fecal elimination accounted for 16% of the dose.

In single-dose studies, the observed elimination half-life (t1/2) was 1.54 ± 0.63 hours. After intravenous administration, total clearance was 0.80 ± 0.24 L/hr/kg (mean ± SD).

Effects of Food on Oral Absorption: Bioavailability of abacavir tablets was assessed in the fasting and fed states. There was no significant difference in systemic exposure (AUC∞) in the fed and fasting states; therefore, ZIAGEN Tablets may be administered with or without food. Systemic exposure to abacavir was comparable after administration of ZIAGEN Oral Solution and ZIAGEN Tablets. Therefore, these products may be used interchangeably.

Special Populations: Renal Impairment: The pharmacokinetic properties of ZIAGEN have not been determined in patients with impaired renal function. Renal excretion of unchanged abacavir is a minor route of elimination in humans.

Hepatic Impairment: The pharmacokinetics of abacavir have been studied in patients with mild hepatic impairment (Child-Pugh score 5 to 6). Results showed that there was a mean increase of 89% in the abacavir AUC, and an increase of 58% in the half-life of abacavir after a single dose of 600 mg of abacavir. The AUCs of the metabolites were not modified by mild liver disease; however, the rates of formation and elimination of the metabolites were decreased. A dose of 200 mg (provided by 10 mL of ZIAGEN Oral Solution) administered twice daily is recommended for patients with mild liver disease. The safety, efficacy, and pharmacokinetics of abacavir have not been studied in patients with moderate or severe hepatic impairment, therefore ZIAGEN is contraindicated in these patients.

Pediatric Patients: The pharmacokinetics of abacavir have been studied after either single or repeat doses of ZIAGEN in 68 pediatric patients. Following multiple-dose administration of ZIAGEN 8 mg/kg twice daily, steady-state AUC(0-12 hr) and Cmax were 9.8 ± 4.56 mcg•hr/mL and 3.71 ± 1.36 mcg/mL (mean ± SD), respectively [see Use in Specific Populations (8.4)]. In addition, to support dosing of ZIAGEN scored tablet (300 mg) for pediatric patients 14 to greater than 30 kg, analysis of actual and simulated pharmacokinetic data indicated comparable exposures are expected following administration of 300 mg scored tablet and the 8 mg/kg dosing regimen using oral solution.

Geriatric Patients: The pharmacokinetics of ZIAGEN have not been studied in patients over 65 years of age.

Gender: A population pharmacokinetic analysis in HIV-1-infected male (n = 304) and female (n = 67) patients showed no gender differences in abacavir AUC normalized for lean body weight.

Race: There are no significant differences between blacks and Caucasians in abacavir pharmacokinetics.

Drug Interactions: In human liver microsomes, abacavir did not inhibit cytochrome P450 isoforms (2C9, 2D6, 3A4). Based on these data, it is unlikely that clinically significant drug interactions will occur between abacavir and drugs metabolized through these pathways.

Lamivudine and/or Zidovudine: Due to the common metabolic pathways of abacavir and zidovudine via glucuronyl transferase, 15 HIV-1-infected patients were enrolled in a crossover study evaluating single doses of abacavir (600 mg), lamivudine (150 mg), and zidovudine (300 mg) alone or in combination. Analysis showed no clinically relevant changes in the pharmacokinetics of abacavir with the addition of lamivudine or zidovudine or the combination of lamivudine and zidovudine. Lamivudine exposure (AUC decreased 15%) and zidovudine exposure (AUC increased 10%) did not show clinically relevant changes with concurrent abacavir.

Ethanol: Due to their common metabolic pathways via alcohol dehydrogenase, the pharmacokinetic interaction between abacavir and ethanol was studied in 24 HIV-1-infected male patients. Each patient received the following treatments on separate occasions: a single 600-mg dose of abacavir, 0.7 g/kg ethanol (equivalent to 5 alcoholic drinks), and abacavir 600 mg plus 0.7 g/kg ethanol. Coadministration of ethanol and abacavir resulted in a 41% increase in abacavir AUC∞ and a 26% increase in abacavir t1/2. In males, abacavir had no effect on the pharmacokinetic properties of ethanol, so no clinically significant interaction is expected in men. This interaction has not been studied in females.

Methadone: In a study of 11 HIV-1-infected patients receiving methadone-maintenance therapy (40 mg and 90 mg daily), with 600 mg of ZIAGEN twice daily (twice the currently recommended dose), oral methadone clearance increased 22% (90% CI 6% to 42%). This alteration will not result in a methadone dose modification in the majority of patients; however, an increased methadone dose may be required in a small number of patients. The addition of methadone had no clinically significant effect on the pharmacokinetic properties of abacavir.

12.4 Microbiology

Abacavir is a carbocyclic synthetic nucleoside analogue. Abacavir is converted by cellular enzymes to the active metabolite, carbovir triphosphate (CBV-TP), an analogue of deoxyguanosine-5′-triphosphate (dGTP). CBV-TP inhibits the activity of HIV-1 reverse transcriptase (RT) both by competing with the natural substrate dGTP and by its incorporation into viral DNA. The lack of a 3′-OH group in the incorporated nucleotide analogue prevents the formation of the 5′ to 3′ phosphodiester linkage essential for DNA chain elongation, and therefore, the viral DNA growth is terminated. CBV-TP is a weak inhibitor of cellular DNA polymerases α, β, and γ.

Antiviral Activity: The antiviral activity of abacavir against HIV-1 was evaluated against a T-cell tropic laboratory strain HIV-1IIIB in lymphoblastic cell lines, a monocyte/macrophage tropic laboratory strain HIV-1BaL in primary monocytes/macrophages, and clinical isolates in peripheral blood mononuclear cells. The concentration of drug necessary to effect viral replication by 50 percent (EC50) ranged from 3.7 to 5.8 μM (1 μM = 0.28 mcg/mL) and 0.07 to 1.0 μM against HIV-1IIIB and HIV-1BaL, respectively, and was 0.26 ± 0.18 μM against 8 clinical isolates. The EC50 values of abacavir against different HIV-1 clades (A-G) ranged from 0.0015 to 1.05 μM, and against HIV-2 isolates, from 0.024 to 0.49 μM. Abacavir had synergistic activity in cell culture in combination with the nucleoside reverse transcriptase inhibitor (NRTI) zidovudine, the non-nucleoside reverse transcriptase inhibitor (NNRTI) nevirapine, and the protease inhibitor (PI) amprenavir; and additive activity in combination with the NRTIs didanosine, emtricitabine, lamivudine, stavudine, tenofovir, and zalcitabine. Ribavirin (50 μM) had no effect on the anti–HIV-1 activity of abacavir in cell culture.

Resistance: HIV-1 isolates with reduced susceptibility to abacavir have been selected in cell culture and were also obtained from patients treated with abacavir. Genotypic analysis of isolates selected in cell culture and recovered from abacavir-treated patients demonstrated that amino acid substitutions K65R, L74V, Y115F, and M184V/I in RT contributed to abacavir resistance. In a study of therapy-naive adults receiving ZIAGEN 600 mg once daily (n = 384) or 300 mg twice daily (n = 386), in a background regimen of lamivudine 300 mg once daily and efavirenz 600 mg once daily (CNA30021), the incidence of virologic failure at 48 weeks was similar between the 2 groups (11% in both arms). Genotypic (n = 38) and phenotypic analyses (n = 35) of virologic failure isolates from this study showed that the RT substitutions that emerged during abacavir once-daily and twice-daily therapy were K65R, L74V, Y115F, and M184V/I. The substitution M184V/I was the most commonly observed substitution in virologic failure isolates from patients receiving abacavir once daily (56%, 10/18) and twice daily (40%, 8/20).

Thirty-nine percent (7/18) of the isolates from patients who experienced virologic failure in the abacavir once-daily arm had a greater than 2.5-fold decrease in abacavir susceptibility with a median-fold decrease of 1.3 (range 0.5 to 11) compared with 29% (5/17) of the failure isolates in the twice-daily arm with a median-fold decrease of 0.92 (range 0.7 to 13).

Cross-Resistance: Cross-resistance has been observed among NRTIs. Isolates containing abacavir resistance-associated substitutions, namely, K65R, L74V, Y115F, and M184V, exhibited cross-resistance to didanosine, emtricitabine, lamivudine, tenofovir, and zalcitabine in cell culture and in patients. The K65R substitution can confer resistance to abacavir, didanosine, emtricitabine, lamivudine, stavudine, tenofovir, and zalcitabine; the L74V substitution can confer resistance to abacavir, didanosine, and zalcitabine; and the M184V substitution can confer resistance to abacavir, didanosine, emtricitabine, lamivudine, and zalcitabine. An increasing number of thymidine analogue mutations (TAMs: M41L, D67N, K70R, L210W, T215Y/F, K219E/R/H/Q/N) is associated with a progressive reduction in abacavir susceptibility.

13 NONCLINICAL TOXICOLOGY

13.1 Carcinogenesis, Mutagenesis, Impairment of Fertility

Abacavir was administered orally at 3 dosage levels to separate groups of mice and rats in 2-year carcinogenicity studies. Results showed an increase in the incidence of malignant and non-malignant tumors. Malignant tumors occurred in the preputial gland of males and the clitoral gland of females of both species, and in the liver of female rats. In addition, non-malignant tumors also occurred in the liver and thyroid gland of female rats. These observations were made at systemic exposures in the range of 6 to 32 times the human exposure at the recommended dose. It is not known how predictive the results of rodent carcinogenicity studies may be for humans.

Abacavir induced chromosomal aberrations both in the presence and absence of metabolic activation in an in vitro cytogenetic study in human lymphocytes. Abacavir was mutagenic in the absence of metabolic activation, although it was not mutagenic in the presence of metabolic activation in an L5178Y mouse lymphoma assay. Abacavir was clastogenic in males and not clastogenic in females in an in vivo mouse bone marrow micronucleus assay.

Abacavir was not mutagenic in bacterial mutagenicity assays in the presence and absence of metabolic activation.

Abacavir had no adverse effects on the mating performance or fertility of male and female rats at a dose approximately 8 times the human exposure at the recommended dose based on body surface area comparisons.

13.2 Animal Toxicology and/or Pharmacology

Myocardial degeneration was found in mice and rats following administration of abacavir for 2 years. The systemic exposures were equivalent to 7 to 24 times the expected systemic exposure in humans. The clinical relevance of this finding has not been determined.

14 CLINICAL STUDIES

14.1 Adults

Therapy-Naive Adults: CNA30024 was a multicenter, double-blind, controlled study in which 649 HIV-1-infected, therapy-naive adults were randomized and received either ZIAGEN (300 mg twice daily), lamivudine (150 mg twice daily), and efavirenz (600 mg once daily) or zidovudine (300 mg twice daily), lamivudine (150 mg twice daily), and efavirenz (600 mg once daily). The duration of double-blind treatment was at least 48 weeks. Study participants were: male (81%), Caucasian (51%), black (21%), and Hispanic (26%). The median age was 35 years, the median pretreatment CD4+ cell count was 264 cells/mm^3, and median plasma HIV-1 RNA was 4.79 log10 copies/mL. The outcomes of randomized treatment are provided in Table 7.

Table 7. Outcomes of Randomized Treatment Through Week 48 (CNA30024)
Outcome | ZIAGEN plus Lamivudine plus Efavirenz; (n = 324) | Zidovudine plus Lamivudine plus Efavirenz; (n = 325)
Responder* | 69% (73%) | 69% (71%)
Virologic failures† | 6% | 4%
Discontinued due to adverse reactions | 14% | 16%
Discontinued due to other reasons‡ | 10% | 11%
* Patients achieved and maintained confirmed HIV-1 RNA ≤50 copies/mL (<400 copies/mL) through Week 48 (Roche AMPLICOR Ultrasensitive HIV-1 MONITOR® standard test 1.0 PCR).
† Includes viral rebound, insufficient viral response according to the investigator, and failure to achieve confirmed ≤50 copies/mL by Week 48.
‡ Includes consent withdrawn, lost to follow up, protocol violations, those with missing data, clinical progression, and other.

After 48 weeks of therapy, the median CD4+ cell count increases from baseline were 209 cells/mm^3 in the group receiving ZIAGEN and 155 cells/mm^3 in the zidovudine group. Through Week 48, 8 subjects (2%) in the group receiving ZIAGEN (5 CDC classification C events and 3 deaths) and 5 subjects (2%) on the zidovudine arm (3 CDC classification C events and 2 deaths) experienced clinical disease progression.

CNA3005 was a multicenter, double-blind, controlled study in which 562 HIV-1-infected, therapy-naive adults were randomized to receive either ZIAGEN (300 mg twice daily) plus COMBIVIR (lamivudine 150 mg/zidovudine 300 mg twice daily), or indinavir (800 mg 3 times a day) plus COMBIVIR twice daily. The study was stratified at randomization by pre-entry plasma HIV-1 RNA 10,000 to 100,000 copies/mL and plasma HIV-1 RNA greater than 100,000 copies/mL. Study participants were male (87%), Caucasian (73%), black (15%), and Hispanic (9%). At baseline the median age was 36 years, the median baseline CD4+ cell count was 360 cells/mm^3, and median baseline plasma HIV-1 RNA was 4.8 log10 copies/mL. Proportions of patients with plasma HIV-1 RNA less than 400 copies/mL (using Roche AMPLICOR HIV-1 MONITOR Test) through 48 weeks of treatment are summarized in Table 8.

Table 8. Outcomes of Randomized Treatment Through Week 48 (CNA3005)
Outcome | ZIAGEN plus Lamivudine/Zidovudine; (n = 262) | Indinavir plus; Lamivudine/Zidovudine; (n = 265)
Responder* | 49% | 50%
Virologic failure† | 31% | 28%
Discontinued due to adverse reactions | 10% | 12%
Discontinued due to other reasons‡ | 11% | 10%
* Patients achieved and maintained confirmed HIV-1 RNA <400 copies/mL.
† Includes viral rebound and failure to achieve confirmed <400 copies/mL by Week 48.
‡ Includes consent withdrawn, lost to follow up, protocol violations, those with missing data, clinical progression, and other.

Treatment response by plasma HIV-1 RNA strata is shown in Table 9.

Table 9. Proportions of Responders Through Week 48 By Screening Plasma HIV-1 RNA Levels (CNA3005)
Screening; HIV-1 RNA; (copies/mL) | ZIAGEN plus Lamivudine/Zidovudine; (n = 262) |  | Indinavir plus; Lamivudine/Zidovudine; (n = 265)
Screening; HIV-1 RNA; (copies/mL) | <400 copies/mL | n | <400 copies/mL | n
≥10,000 - ≤100,000 | 50% | 166 | 48% | 165
>100,000 | 48% | 96 | 52% | 100

In subjects with baseline viral load greater than 100,000 copies/mL, percentages of patients with HIV-1 RNA levels less than 50 copies/mL were 31% in the group receiving abacavir vs. 45% in the group receiving indinavir.

Through Week 48, an overall mean increase in CD4+ cell count of about 150 cells/mm^3 was observed in both treatment arms. Through Week 48, 9 subjects (3.4%) in the group receiving abacavir sulfate (6 CDC classification C events and 3 deaths) and 3 subjects (1.5%) in the group receiving indinavir (2 CDC classification C events and 1 death) experienced clinical disease progression.

CNA30021 was an international, multicenter, double-blind, controlled study in which 770 HIV-1-infected, therapy-naive adults were randomized and received either abacavir 600 mg once daily or abacavir 300 mg twice daily, both in combination with lamivudine 300 mg once daily and efavirenz 600 mg once daily. The double-blind treatment duration was at least 48 weeks. Study participants had a mean age of 37 years, were: male (81%), Caucasian (54%), black (27%), and American Hispanic (15%). The median baseline CD4+ cell count was 262 cells/mm^3 (range 21 to 918 cells/mm^3) and the median baseline plasma HIV-1 RNA was 4.89 log10 copies/mL (range: 2.60 to 6.99 log10 copies/mL).

The outcomes of randomized treatment are provided in Table 10.

Table 10. Outcomes of Randomized Treatment Through Week 48 (CNA30021)
Outcome | ZIAGEN 600 mg q.d. plus EPIVIR plus Efavirenz; (n = 384) | ZIAGEN 300 mg b.i.d. plus EPIVIR plus Efavirenz; (n = 386)
Responder* | 64% (71%) | 65% (72%)
Virologic failure† | 11% (5%) | 11% (5%)
Discontinued due to adverse reactions | 13% | 11%
Discontinued due to other reasons‡ | 11% | 13%
* Patients achieved and maintained confirmed HIV-1 RNA <50 copies/mL (<400 copies/mL) through Week 48 (Roche AMPLICOR Ultrasensitive HIV-1 MONITOR standard test version 1.0).
† Includes viral rebound, failure to achieve confirmed <50 copies/mL (<400 copies/mL) by Week 48, and insufficient viral load response.
‡ Includes consent withdrawn, lost to follow up, protocol violations, clinical progression, and other.

After 48 weeks of therapy, the median CD4+ cell count increases from baseline were 188 cells/mm^3 in the group receiving abacavir 600 mg once daily and 200 cells/mm^3 in the group receiving abacavir 300 mg twice daily. Through Week 48, 6 subjects (2%) in the group receiving ZIAGEN 600 mg once daily (4 CDC classification C events and 2 deaths) and 10 subjects (3%) in the group receiving ZIAGEN 300 mg twice daily (7 CDC classification C events and 3 deaths) experienced clinical disease progression. None of the deaths were attributed to study medications.

14.2 Pediatric Patients

Therapy-Experienced Pediatric Patients: CNA3006 was a randomized, double-blind study comparing ZIAGEN 8 mg/kg twice daily plus lamivudine 4 mg/kg twice daily plus zidovudine 180 mg/m^2 twice daily versus lamivudine 4 mg/kg twice daily plus zidovudine 180 mg/m^2 twice daily. Two hundred and five therapy-experienced pediatric patients were enrolled: female (56%), Caucasian (17%), black (50%), Hispanic (30%), median age of 5.4 years, baseline CD4+ cell percent greater than 15% (median = 27%), and median baseline plasma HIV-1 RNA of 4.6 log10 copies/mL. Eighty percent and 55% of patients had prior therapy with zidovudine and lamivudine, respectively, most often in combination. The median duration of prior nucleoside analogue therapy was 2 years. At 16 weeks the proportion of patients responding based on plasma HIV-1 RNA less than or equal to 400 copies/mL was significantly higher in patients receiving ZIAGEN plus lamivudine plus zidovudine compared with patients receiving lamivudine plus zidovudine, 13% versus 2%, respectively. Median plasma HIV-1 RNA changes from baseline were -0.53 log10 copies/mL in the group receiving ZIAGEN plus lamivudine plus zidovudine compared with -0.21 log10 copies/mL in the group receiving lamivudine plus zidovudine. Median CD4+ cell count increases from baseline were 69 cells/mm^3 in the group receiving ZIAGEN plus lamivudine plus zidovudine and 9 cells/mm^3 in the group receiving lamivudine plus zidovudine.

15 REFERENCES

1. Data Collection on Adverse Events of Anti-HIV Drugs (D:A:D) Study Group. Lancet. 2008;371 (9622):1417-1426.

16 HOW SUPPLIED/STORAGE AND HANDLING

ZIAGEN Tablets, containing abacavir sulfate equivalent to 300 mg abacavir are yellow, biconvex, scored, capsule-shaped, film-coated, and imprinted with “GX 623” on both sides.

They are supplied by State of Florida DOH Central Pharmacy as follows:

NDC | Strength | Quantity/Form | Color | Source Prod. Code
53808-0811-1 | 300 mg | 1 Tablet in a Blister Pack | YELLOW | 0173-0661

Store at controlled room temperature of 20° to 25°C (68° to 77°F) (see USP).

ZIAGEN Oral Solution is a clear to opalescent, yellowish, strawberry-banana-flavored liquid. Each mL of the solution contains abacavir sulfate equivalent to 20 mg of abacavir. It is packaged in plastic bottles as follows:

Bottles of 240 mL (NDC 0173-0664-00) with child-resistant closure. This product does not require reconstitution.

Store at controlled room temperature of 20° to 25°C (68° to 77°F) (see USP). DO NOT FREEZE. May be refrigerated.

17 PATIENT COUNSELING INFORMATION

See Medication Guide. (17.2)

17.1 Information About Therapy With ZIAGEN

Hypersensitivity Reaction: Inform patients:

- that a Medication Guide and Warning Card summarizing the symptoms of the abacavir hypersensitivity reaction and other product information will be dispensed by the pharmacist with each new prescription and refill of ZIAGEN, and encourage the patient to read the Medication Guide and Warning Card every time to obtain any new information that may be present about ZIAGEN. (The complete text of the Medication Guide is reprinted at the end of this document.)
- to carry the Warning Card with them.
- how to identify a hypersensitivity reaction [see Medication Guide (17.2)].
- that if they develop symptoms consistent with a hypersensitivity reaction they should call their doctor right away to determine if they should stop taking ZIAGEN.
- that a hypersensitivity reaction can worsen and lead to hospitalization or death if ZIAGEN is not immediately discontinued.
- that in one study, more severe hypersensitivity reactions were seen when ZIAGEN was dosed 600 mg once daily.
- to not restart ZIAGEN or any other abacavir-containing product following a hypersensitivity reaction because more severe symptoms can occur within hours and may include life-threatening hypotension and death.
- that a hypersensitivity reaction is usually reversible if it is detected promptly and ZIAGEN is stopped right away.
- that if they have interrupted ZIAGEN for reasons other than symptoms of hypersensitivity (for example, those who have an interruption in drug supply), a serious or fatal hypersensitivity reaction may occur with reintroduction of abacavir.
- to not restart ZIAGEN or any other abacavir-containing product without medical consultation and that restarting abacavir needs to be undertaken only if medical care can be readily accessed by the patient or others.
- ZIAGEN should not be coadministered with EPZICOM® or TRIZIVIR®.

Lactic Acidosis/Hepatomegaly: Inform patients that some HIV medicines, including ZIAGEN, can cause a rare, but serious condition called lactic acidosis with liver enlargement (hepatomegaly).

Redistribution/Accumulation of Body Fat: Inform patients that redistribution or accumulation of body fat may occur in patients receiving antiretroviral therapy and that the cause and long-term health effects of these conditions are not known at this time.

Information About HIV-1 Infection: ZIAGEN is not a cure for HIV -1 infection and patients may continue to experience illnesses associated with HIV-1 infection, including opportunistic infections. Patients should remain under the care of a physician when using ZIAGEN. Advise patients that the use of ZIAGEN has not been shown to reduce the risk of transmission of HIV-1 to others through sexual contact or blood contamination. Patients should be informed to take all HIV medications exactly as prescribed.

MEDICATION GUIDE

ZIAGEN® (ZY-uh-jen) Tablets

ZIAGEN® Oral Solution

Generic name: abacavir (uh-BACK-ah-veer) sulfate tablets and oral solution

Read the Medication Guide that comes with ZIAGEN before you start taking it and each time you get a refill because there may be new information. This information does not take the place of talking to your doctor about your medical condition or your treatment. Be sure to carry your ZIAGEN Warning Card with you at all times.

What is the most important information I should know about ZIAGEN?

- Serious Allergic Reaction to Abacavir. ZIAGEN contains abacavir (also contained in EPZICOM® and TRIZIVIR®). Patients taking ZIAGEN may have a serious allergic reaction (hypersensitivity reaction) that can cause death. Your risk of this allergic reaction is much higher if you have a gene variation called HLA-B*5701 than if you do not. Your doctor can determine with a blood test if you have this gene variation. If you get a symptom from 2 or more of the following groups while taking ZIAGEN, call your doctor right away to determine if you should stop taking this medicine.

 | Symptom(s)
Group 1 | Fever
Group 2 | Rash
Group 3 | Nausea, vomiting, diarrhea, abdominal (stomach area) pain
Group 4 | Generally ill feeling, extreme tiredness, or achiness
Group 5 | Shortness of breath, cough, sore throat

A list of these symptoms is on the Warning Card your pharmacist gives you. Carry this Warning Card with you.

If you stop ZIAGEN because of an allergic reaction, NEVER take ZIAGEN (abacavir sulfate) or any other abacavir-containing medicine (EPZICOM and TRIZIVIR) again. If you take ZIAGEN or any other abacavir-containing medicine again after you have had an allergic reaction, WITHIN HOURS you may get life-threatening symptoms that may include very low blood pressure or death.

If you stop ZIAGEN for any other reason, even for a few days and you are not allergic to ZIAGEN, talk with your doctor before taking it again. Taking ZIAGEN again can cause a serious allergic or life-threatening reaction, even if you never had an allergic reaction to it before. If your doctor tells you that you can take ZIAGEN again, start taking it when you are around medical help or people who can call a doctor if you need one.

- Lactic Acidosis. Some human immunodeficiency virus (HIV) medicines, including ZIAGEN, can cause a rare but serious condition called lactic acidosis with liver enlargement (hepatomegaly). Nausea and tiredness that don't get better may be symptoms of lactic acidosis. In some cases this condition can cause death. Women, overweight people, and people who have taken HIV medicines like ZIAGEN for a long time have a higher chance of getting lactic acidosis and liver enlargement. Lactic acidosis is a medical emergency and must be treated in the hospital.

ZIAGEN can have other serious side effects. Be sure to read the section below entitled "What are the possible side effects of ZIAGEN?"

What is ZIAGEN?

ZIAGEN is a prescription medicine used to treat HIV infection. ZIAGEN is taken by mouth as a tablet or a strawberry-banana-flavored liquid. ZIAGEN is a medicine called a nucleoside analogue reverse transcriptase inhibitor (NRTI). ZIAGEN is always used with other anti-HIV medicines. When used in combination with these other medicines, ZIAGEN helps lower the amount of HIV found in your blood. This helps to keep your immune system as healthy as possible so that it can help fight infection.

Different combinations of medicines are used to treat HIV infection. You and your doctor should discuss which combination of medicines is best for you.

- ZIAGEN does not cure HIV infection or AIDS. We do not know if ZIAGEN will help you live longer or have fewer of the medical problems that people get with HIV or AIDS. It is very important that you see your doctor regularly while you are taking ZIAGEN.
- ZIAGEN does not lower the risk of passing HIV to other people through sexual contact, sharing needles, or being exposed to your blood. For your health and the health of others, it is important to always practice safe sex by using a latex or polyurethane condom or other barrier method to lower the chance of sexual contact with semen, vaginal secretions, or blood. Never use or share dirty needles.

ZIAGEN has not been studied in children under 3 months of age or in adults over 65 years of age.

Who should not take ZIAGEN?

Do not take ZIAGEN if you:

- have ever had a serious allergic reaction (a hypersensitivity reaction) to ZIAGEN or any other medicine that has abacavir as one of its ingredients (EPZICOM and TRIZIVIR). See the end of this Medication Guide for a complete list of ingredients in ZIAGEN.
- have a liver that does not function properly.

Before starting ZIAGEN, tell your doctor about all of your medical conditions, including if you:

- have been tested and know whether or not you have a particular gene variation called HLA-B*5701.
- are pregnant or planning to become pregnant. We do not know if ZIAGEN will harm your unborn child. You and your doctor will need to decide if ZIAGEN is right for you. If you use ZIAGEN while you are pregnant, talk to your doctor about how you can be on the Antiviral Pregnancy Registry for ZIAGEN.
- are breastfeeding. We do not know if ZIAGEN can be passed to your baby in your breast milk and whether it could harm your baby. Also, mothers with HIV should not breastfeed because HIV can be passed to the baby in the breast milk.
- have liver problems.
- have heart problems, smoke, or suffer from diseases that increase your risk of heart disease such as high blood pressure, high cholesterol, or diabetes.

Tell your doctor about all the medicines you take, including prescription and nonprescription medicines, vitamins, and herbal supplements. Especially tell your doctor if you take:

- methadone
- EPZICOM (abacavir sulfate and lamivudine) and TRIZIVIR (abacavir sulfate, lamivudine, and zidovudine).

How should I take ZIAGEN?

- Take ZIAGEN by mouth exactly as your doctor prescribes it. Your doctor will tell you the right dose to take. The usual doses are 1 tablet twice a day or 2 tablets once a day. Do not skip doses.
- Children aged 3 months and older can also take ZIAGEN. The child's healthcare professional will decide the right dose and formulation based on the child's weight. The dose should not exceed the recommended adult dose.
- You can take ZIAGEN with or without food.
- If you miss a dose of ZIAGEN, take the missed dose right away. Then, take the next dose at the usual time.
- Do not let your ZIAGEN run out.
- Starting ZIAGEN again can cause a serious allergic or life-threatening reaction, even if you never had an allergic reaction to it before. If you run out of ZIAGEN even for a few days, you must ask your doctor if you can start ZIAGEN again. If your doctor tells you that you can take ZIAGEN again, start taking it when you are around medical help or people who can call a doctor if you need one.
- If you stop your anti-HIV drugs, even for a short time, the amount of virus in your blood may increase and the virus may become harder to treat.
- If you take too much ZIAGEN, call your doctor or poison control center right away.

What should I avoid while taking ZIAGEN?

- Do not take EPZICOM (abacavir sulfate and lamivudine) or TRIZIVIR (abacavir sulfate, lamivudine, and zidovudine) while taking ZIAGEN. Some of these medicines are already in ZIAGEN.

Avoid doing things that can spread HIV infection, as ZIAGEN does not stop you from passing the HIV infection to others.

- Do not share needles or other injection equipment.
- Do not share personal items that can have blood or body fluids on them, like toothbrushes and razor blades.
- Do not have any kind of sex without protection. Always practice safe sex by using a latex or polyurethane condom or other barrier method to lower the chance of sexual contact with semen, vaginal secretions, or blood.
- Do not breastfeed. We do not know if ZIAGEN can be passed to your baby in your breast milk and whether it could harm your baby. Also, mothers with HIV should not breastfeed because HIV can be passed to the baby in the breast milk.

What are the possible side effects of ZIAGEN?

ZIAGEN can cause the following serious side effects:

- Serious allergic reaction that can cause death. (See "What is the most important information I should know about ZIAGEN?" at the beginning of this Medication Guide.)
- Lactic acidosis with liver enlargement (hepatomegaly) that can cause death. (See "What is the most important information I should know about ZIAGEN?" at the beginning of this Medication Guide.)
- Changes in immune system. When you start taking HIV medicines, your immune system may get stronger and could begin to fight infections that have been hidden in your body, such as pneumonia, herpes virus, or tuberculosis. If you have new symptoms after starting your HIV medicines, be sure to tell your doctor.
- Changes in body fat. These changes have happened in patients taking antiretroviral medicines like ZIAGEN. The changes may include an increased amount of fat in the upper back and neck (“buffalo hump”), breast, and around the back, chest, and stomach area. Loss of fat from the legs, arms, and face may also happen. The cause and long-term health effects of these conditions are not known.

Some HIV medicines including ZIAGEN may increase your risk of heart attack. If you have heart problems, smoke, or suffer from diseases that increase your risk of heart disease such as high blood pressure, high cholesterol, or diabetes, tell your doctor.

The most common side effects of ZIAGEN include nausea, vomiting, tiredness, headache, diarrhea, trouble sleeping, fever and chills, and loss of appetite. Most of these side effects did not cause people to stop taking ZIAGEN.

This list of side effects is not complete. Call your doctor for medical advice about side effects. You may report side effects to FDA at 1-800-FDA-1088.

How should I store ZIAGEN?

- Store ZIAGEN at room temperature, between 68° to 77°F (20° to 25°C). Do not freeze ZIAGEN.
- Keep ZIAGEN and all medicines out of the reach of children.

General information for safe and effective use of ZIAGEN

Medicines are sometimes prescribed for conditions that are not mentioned in Medication Guides. Do not use ZIAGEN for a condition for which it was not prescribed. Do not give ZIAGEN to other people, even if they have the same symptoms that you have. It may harm them.

This Medication Guide summarizes the most important information about ZIAGEN. If you would like more information, talk with your doctor. You can ask your doctor or pharmacist for the information that is written for healthcare professionals or call 1-888-825-5249.

What are the ingredients in ZIAGEN?

Tablets: Each tablet contains abacavir sulfate equivalent to 300 mg of abacavir as active ingredient and the following inactive ingredients: colloidal silicon dioxide, magnesium stearate, microcrystalline cellulose, and sodium starch glycolate. The film-coating is made of hypromellose, polysorbate 80, synthetic yellow iron oxide, titanium dioxide, and triacetin.

Oral Solution: Each milliliter (1 mL) of ZIAGEN Oral Solution contains abacavir sulfate equivalent to 20 mg of abacavir (i.e., 20 mg/mL) as active ingredient and the following inactive ingredients: artificial strawberry and banana flavors, citric acid (anhydrous), methylparaben and propylparaben (added as preservatives), propylene glycol, saccharin sodium, sodium citrate (dihydrate), sorbitol solution, and water.

This Medication Guide has been approved by the US Food and Drug Administration.

GlaxoSmithKline
Research Triangle Park, NC 27709

©2009, GlaxoSmithKline. All rights reserved.

This Product was Repackaged By:

State of Florida DOH Central Pharmacy
104-2 Hamilton Park Drive
Tallahassee, FL 32304
United States

PACKAGE LABEL

PRINCIPAL DISPLAY PANEL

NDC 53808-0811-1

ZIAGEN ®

(abacavir sulfate)

TABLETS

300 mg

Rx only

30 Tablets

Each tablet contains

abacavir sulfate equivalent

to 300 mg of abacavir.

Store at controlled

room temperature of

20° to 25°C (68° to

77°F) (see USP).

See prescribing information

for dosage

information.

Notice to Authorized

Dispenser:

Each time ZIAGEN is

dispensed, give the

patient a Medication

Guide and Warning

Card from the carton.

GlaxoSmithKline

Research Triangle Park, NC 27709

Made in Ireland